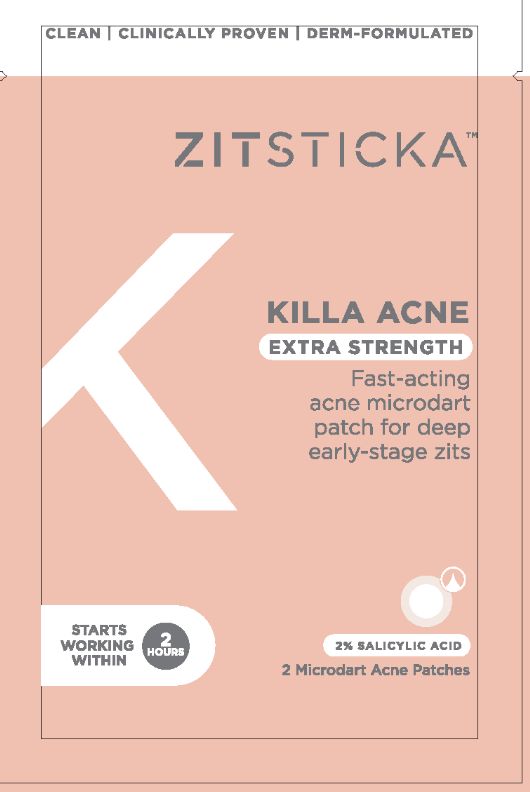 DRUG LABEL: Killa Acne Extra Strength 2 pack
NDC: 81746-899 | Form: PATCH
Manufacturer: ZitSticka, Inc.
Category: otc | Type: HUMAN OTC DRUG LABEL
Date: 20230830

ACTIVE INGREDIENTS: SALICYLIC ACID 0.0125 mg/0.6216 mg
INACTIVE INGREDIENTS: 4-BUTYLRESORCINOL; PHYTOSPHINGOSINE HYDROCHLORIDE; GLYCOLIC ACID; OLIGOPEPTIDE-10; HYALURONATE SODIUM; MADECASSOSIDE; NIACINAMIDE

ACTIVE INGREDIENT

Salicylic Acid 2%

Ask a doctor if irritation become severe.

Keep out of reach of children. If swallowed, get medical help or contact a posion Control Center right away.

Uses:

- For the management of acne.
- Penetrates pores to eliminate most blemishes.

INACTIVE INGREDIENT

Sodium Hyaluronate, phytosphingosine HCl, Niacinamide, Oligopeptide-10, Glycolic Acid, Madecassoside, 4-Butylresorcinol

Uses

- For the management of acne.
- Penetrates pores to eliminate most blemishes.

Directions and How to Use

How to open:

1. To remove a patch, peel the front, top corner and pull towards the center.

2. Inside, you'll find a white tab with a slit on one side. Tear along that seam to reveal the KILLA ACNE Extra Strength patch.

How to use:

1. Cleanse skin thoroughly before applying the product.

2. Once dry, apply KILLA ACNE Extra Strength pimple patch onto zit.

3. Leave on for 2+ hrs for microdarts to dissolve (for best results leave on overnight).

WARNINGS

For external use only.